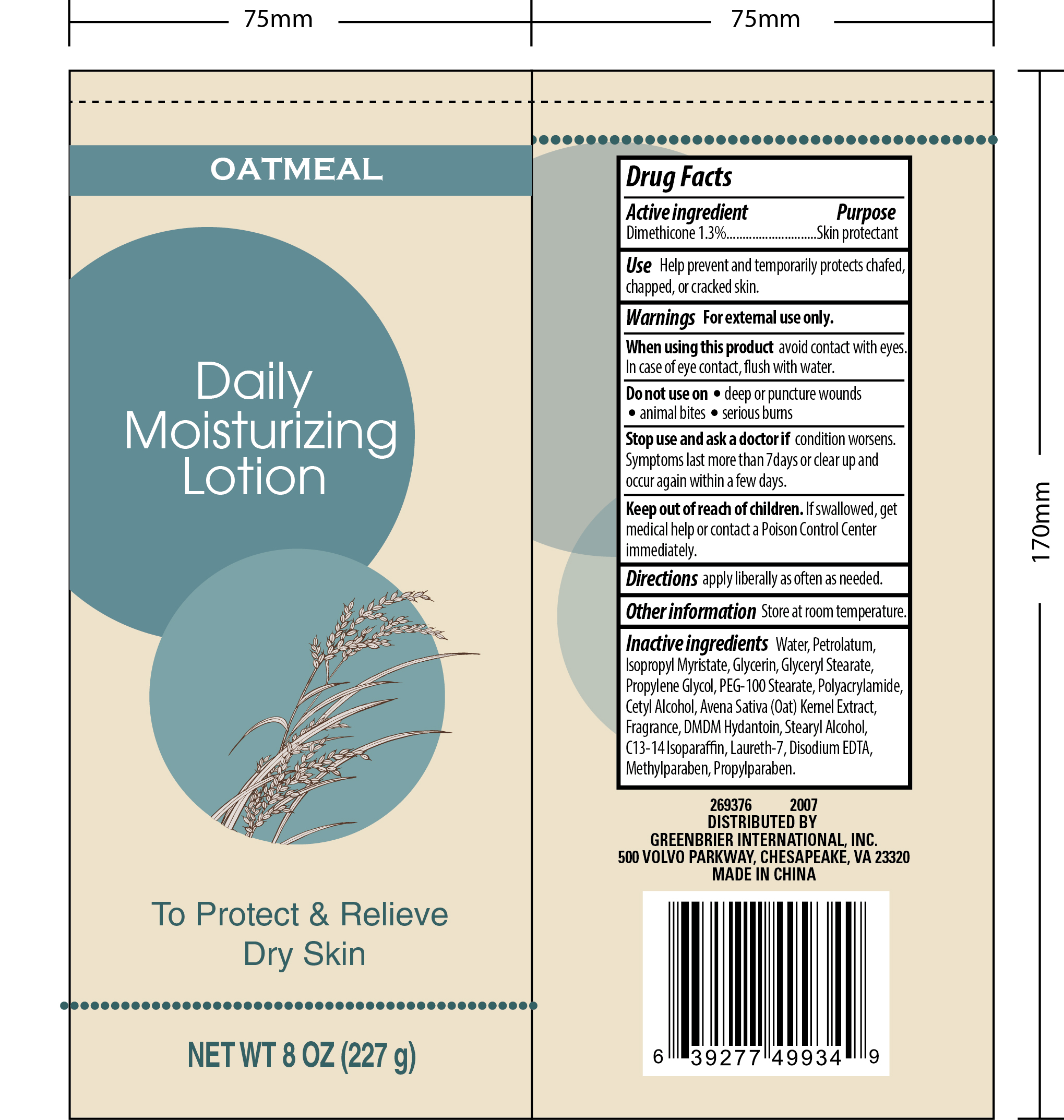 DRUG LABEL: Oatmeal Daily Moisturizing 8oz.
NDC: 55319-514 | Form: LOTION
Manufacturer: Family Dollar Services, Inc.
Category: otc | Type: HUMAN OTC DRUG LABEL
Date: 20200908

ACTIVE INGREDIENTS: DIMETHICONE 3 g/227 g
INACTIVE INGREDIENTS: C13-14 ISOPARAFFIN; METHYLPARABEN; WATER; PETROLATUM; GLYCERIN; PROPYLENE GLYCOL; GLYCERYL MONOSTEARATE; ISOPROPYL MYRISTATE; SODIUM CHLORIDE; BENZYL ALCOHOL; OAT KERNEL OIL; PEG-100 STEARATE; LAURETH-7; PROPYLPARABEN; STEARYL ALCOHOL; POLYACRYLAMIDE (10000 MW); CETYL ALCOHOL; DMDM HYDANTOIN; EDETATE DISODIUM ANHYDROUS

Oatmeal daily moisturizing lotion (8 oz.)

Active Ingredient Purpose

Dimethicone 1.3% ......... Skin Protectant

PURPOSE

Skin protectant

Keep out of reach of children. If swallowed, get medical help or contact a Poison Control Center immediately.

Uses

- Temporarily protects chafed, chapped or cracked skin

Warnings For external use only.

When using this product avoid contact with eyes. In case of eye contact, flush with water.

Stop use and ask a doctor if condition worsens. Symptoms last more than 7 days or clear up and occur again within a few days.

Do not use on

- Deep or puncture wounds
- Animal bites
- Serious burns

DOSAGE AND ADMINISTRATION

Directions apply liberally as often as needed.

Other Information store at room temperature.

DISTRIBUTED BY

GREENBRIER INTERNATIONAL, INC.

500 VOLVO PARKWAY, CHESAPEAKE,VA 23320

MADE IN CHINA

Inactive Ingredients

Water, Petrolatum, Isopropyl Myristate, Glycerin, Glyceryl Stearate, Propylene Glycol, PEG-100 Stearate, Polyacrylamide, Cetyl Alcohol, Avena Sativa (Oat) Kernel Extract, Fragrance, DMDM Hydantoin, Stearyl Alcohol, C13-14 Isoparaffin, Laureth-7, Disodium EDTA, Methylparaben, Propylparaben.